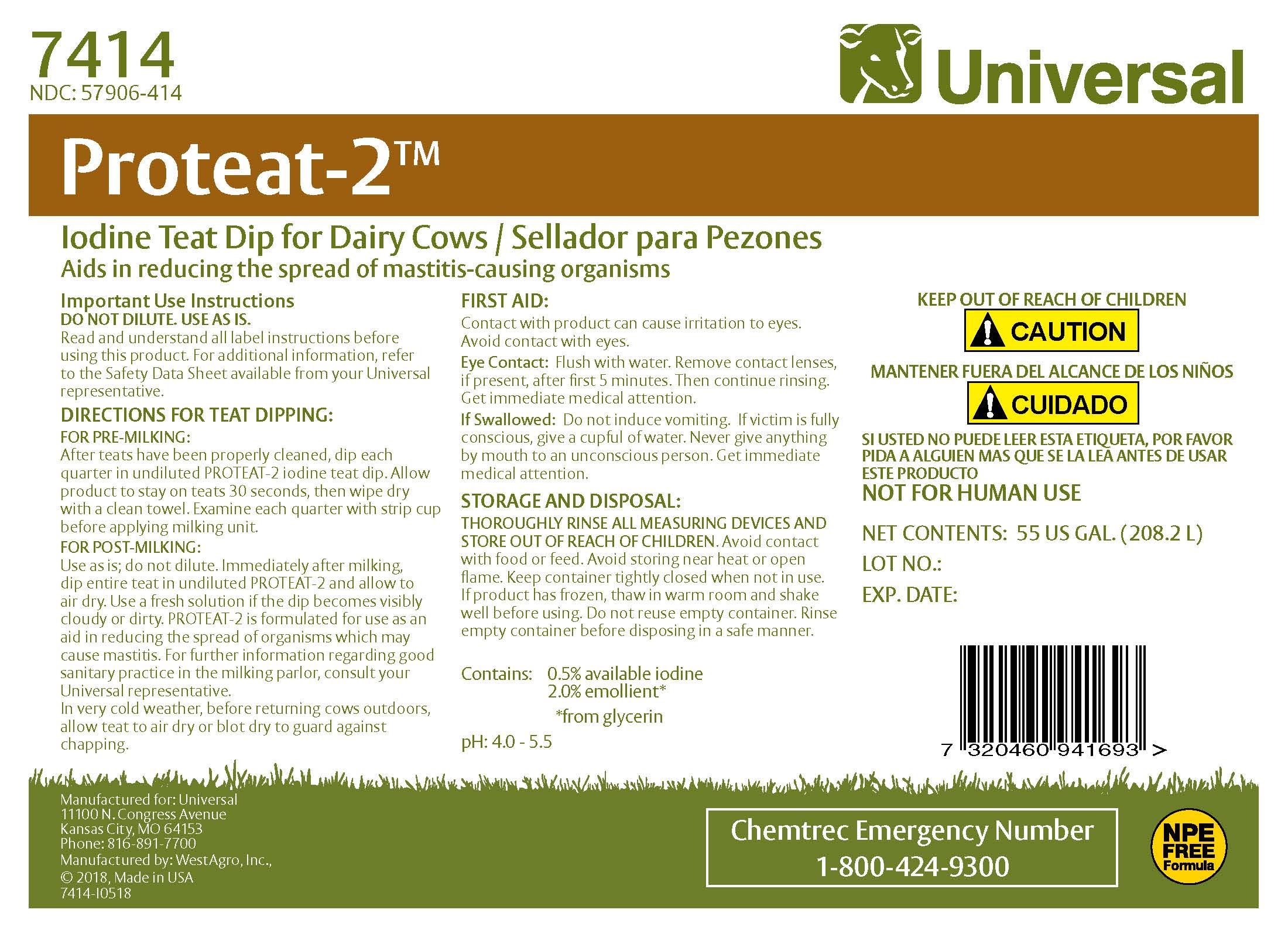 DRUG LABEL: Proteat-2
NDC: 57906-414 | Form: SOLUTION
Manufacturer: Universal
Category: animal | Type: OTC ANIMAL DRUG LABEL
Date: 20230216

ACTIVE INGREDIENTS: IODINE 5.1 g/1 L

Universal Proteat-2

INDICATIONS AND USAGE

Iodine Teat Dip for Dairy Cows / Sellador para Pezones

Important Use Instructions
DO NOT DILUTE. USE AS IS.
Read and understand all label instructions before using this product. For additional information, refer to the Material Safety Data Sheet available from your Universal representative.
DIRECTIONS FOR TEAT DIPPING
FOR PRE-MILKING:
After teats have been properly cleaned, dip each quarter in undiluted PROTEAT-2 iodine teat dip. Allow product to stay on teats 30 seconds, then wipe dry with a clean towel. Examine each quarter with strip cup before applying milking unit.
FOR POST-MILKING:
Use as is; do not dilute. Immediately after milking dip entire teat in undiluted PROTEAT-2 and allow to air dry. Use a fresh solution if the dip becomes visibly cloudy or dirty. PROTEAT-2 is formulated for use as an aid in reducing the spread of organisms which may cause mastitis. For further information regarding good sanitary practices in the milking parlor, consult your Universal representative.

In very cold weather, before returning cows outdoors, allow teats to air dry to guard against chapping.

FIRST AID
Contact with product can cause irritation to eyes. Keep out of eyes.
Eye Contact: Flush with water. Remove contact lenses after first 5 minutes, if present, then continue flushing.
If Swallowed: Drink large quantities of water and induce vomiting.

STORAGE AND DISPOSAL:
THOROUGHLY RINSE ALL MEASURING DEVICES AND STORE OUT OF REACH OF CHILDREN. Avoid contact with food or feed. Avoid storing near heat or open flame. Keep container tightly closed when not in use. If product has frozen, thaw in warm room and shake well before using. Do not reuse empty container. Rinse empty container before disposing in a safe manner.

KEEP OUT OF REACH OF CHILDREN
MANTENER FUERA DEL ALCANCE DE LOS NINOS

!CAUTION !CUIDADO

ACTIVE INGREDIENT

Contains: 0.5% available iodine with an emollient system
pH: 4.0-5.5

Manufactured for: Universal
11100 N. Congress Avenue
Kansas City, MO 64153
Phone: 816-891-7700
Manufactured by: WestAgro, Inc.
©2018, Made in USA

Chemtrec Emergency Number
1-800-424-9300

Net Contents:

Lot No.:

Exp. Date: